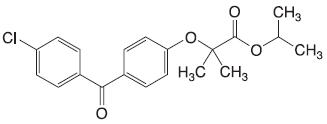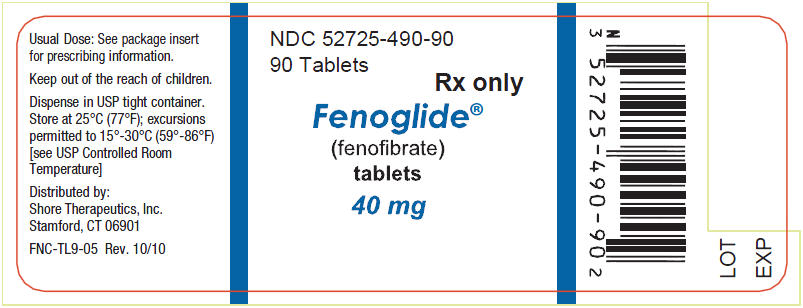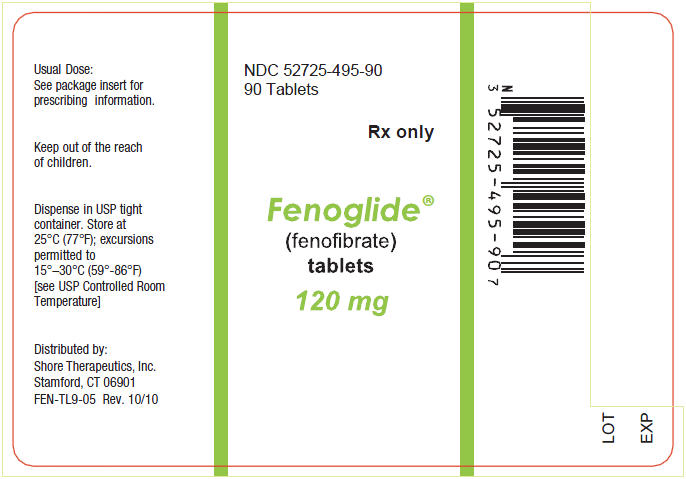 DRUG LABEL: Fenoglide
NDC: 52725-490 | Form: TABLET
Manufacturer: Shore Therapeutics, Inc
Category: prescription | Type: HUMAN PRESCRIPTION DRUG LABEL
Date: 20110513

ACTIVE INGREDIENTS: fenofibrate 40 mg/1 1
INACTIVE INGREDIENTS: lactose monohydrate; Polyethylene Glycol 6000; Poloxamer 188; magnesium stearate

HIGHLIGHTS OF PRESCRIBING INFORMATION

These highlights do not include all the information needed to use Fenoglide® safely and effectively. See full prescribing information for Fenoglide.
Fenoglide (fenofibrate) Tablets
Initial U.S. Approval: 1993

1 INDICATIONS AND USAGE

Fenoglide is a peroxisome proliferator receptor alpha (PPARα) activator indicated:

- as an adjunct to diet to reduce elevated LDL-C, Total-C, TG, and Apo B, and to increase HDL-C in patients with primary hyperlipidemia or mixed dyslipidemia when response to diet and non-pharmacological interventions alone has been inadequate. (1.1)
- as an adjunct to diet to treat patients with hypertriglyceridemia. Improving glycemic control in diabetic patients showing fasting chylomicronemia will usually obviate the need for pharmacologic intervention. (1.2)

Fenofibrate was not shown to reduce coronary heart disease morbidity and mortality in a large, randomized controlled trial of patients with type 2 diabetes mellitus. (1.3)

2 DOSAGE AND ADMINISTRATION

- Primary hyperlipidemia and mixed dyslipidemia: 120 mg/day (2.1)
- Hypertriglyceridemia: 40 to 120 mg/day; the dose should be adjusted according to patient response (2.2)
- Renally impaired patients: 40 mg/day; the dose should be increased according to the effect on renal function and lipid levels (2.4)

To increase absorption of Fenoglide, take with food.

3 DOSAGE FORMS AND STRENGTHS

- 40 mg: White to off-white oval tablets. Debossed "FLO".
- 120 mg: White to off-white oval tablets. Debossed "FHI".

4 CONTRAINDICATIONS

- Severe renal dysfunction, including patients receiving dialysis (4, 12.3)
- Active liver disease (4, 5.1)
- Gallbladder disease (4, 5.2)
- Nursing mothers (4, 8.3)

5 WARNINGS AND PRECAUTIONS

- Fenofibrate can increase serum transaminases. Liver tests should be periodically monitored. (5.1)
- Fenofibrate increases cholesterol excretion into the bile, leading to risk of cholelithiasis. If cholelithiasis is suspected, gallbladder studies are indicated. (5.2)
- Exercise caution in concomitant treatment with coumarin anticoagulants. Reduce the dosage of coumarin to maintain the prothrombin time/INR at the desired level to prevent bleeding complications. (5.3)
- Myopathy and rhabdomyolysis have been reported in patients taking fenofibrate. The risk for serious muscle toxicity appears to be increased in elderly patients and in patients with diabetes, renal failure, or hypothyroidism. (5.4)
- Fenofibrate reversibly increases serum creatinine levels. (5.5)

6 ADVERSE REACTIONS

The most common adverse reactions (> 2% and at least 1% greater than placebo) are abnormal liver tests, increased AST, increased ALT, increased CPK, and rhinitis. (6.1)

To report SUSPECTED ADVERSE REACTIONS, contact Shore Therapeutics Drug Safety Department at 1-888-743-0571 or FDA at 1-800-FDA-1088 or www.fda.gov/medwatch.

7 DRUG INTERACTIONS

- Coumarin Anticoagulants (7.1)
- Cyclosporine (7.2)
- HMG-CoA Reductase Inhibitors (7.3)
- Bile-Acid Resins (7.4)

8 USE IN SPECIFIC POPULATIONS

- Geriatric Use: Dose selection for the elderly should be made on the basis of renal function. (8.5)
- Renal impairment: Fenofibrate should be avoided in patients with severe renal impairment and dose reduction is required in patients with mild to moderate renal impairment. (8.6)

FULL PRESCRIBING INFORMATION

1 INDICATIONS AND USAGE

1.1 Hyperlipidemia and Mixed Dyslipidemia

Fenoglide is indicated as adjunctive therapy to diet to reduce elevated LDL-C, Total-C, Triglycerides, and Apo B, and to increase HDL-C in adult patients with primary hyperlipidemia or mixed dyslipidemia. Lipid-altering agents should be used in addition to a diet restricted in saturated fat and cholesterol when response to diet and nonpharmacological interventions alone has been inadequate.

1.2 Hypertriglyceridemia

Fenoglide is also indicated as adjunctive therapy to diet for treatment of adult patients with hypertriglyceridemia. Improving glycemic control in diabetic patients showing fasting chylomicronemia will usually reduce fasting triglycerides and eliminate chylomicronemia thereby obviating the need for pharmacologic intervention.

1.3 General Guidelines

Fenofibrate was not shown to reduce coronary heart disease morbidity and mortality in a large, randomized controlled trial of patients with type 2 diabetes mellitus. [see Warnings and Precautions (5.6).]

Markedly elevated levels of serum triglycerides (e.g. >2,000 mg/dL) may increase the risk of developing pancreatitis. The effect of Fenoglide therapy on reducing this risk has not been adequately studied.

Drug therapy is not indicated for patients who have elevations of chylomicrons and plasma triglycerides, but who have normal levels of very low density lipoprotein (VLDL). Inspection of plasma refrigerated for 14 hours is helpful in distinguishing these patients from those with elevated VLDL.^2

2 DOSAGE AND ADMINISTRATION

2.1 Hyperlipidemia and Mixed Dyslipidemia

The initial dose of Fenoglide is 120 mg per day.

2.2 Hypertriglyceridemia

The initial dose is 40 to 120 mg per day. Dosage should be individualized according to patient response, and should be adjusted if necessary following repeat lipid determinations at 4 to 8 week intervals. The maximum dose is 120 mg per day.

2.3 Renally Impaired Patients

Treatment with Fenoglide should be initiated at a dose of 40 mg/day in patients with mild to moderately impaired renal function, and increased only after evaluation of the effects on renal function and lipid levels at this dose. The use of Fenoglide should be avoided in patients with severely impaired renal function.

2.4 Elderly Patients

Dose selection for the elderly should be made on the basis of renal function. [See Use in Specific Populations (8.5).]

2.5 General Dosing Information

To increase absorption of Fenoglide, take with food.

3 DOSAGE FORMS AND STRENGTHS

- 40 mg: White to off-white oval tablets. Debossed "FLO".
- 120 mg: White to off-white oval tablets. Debossed "FHI".

4 CONTRAINDICATIONS

- Fenoglide is contraindicated in patients with severe renal dysfunction, including those receiving dialysis [see Clinical Pharmacology (12.3).]
- Fenoglide is contraindicated in patients with active liver disease, including those with primary biliary cirrhosis and unexplained persistent liver function abnormalities [see Warnings and Precautions (5.1).]
- Fenoglide is contraindicated in patients with gallbladder disease [see Warnings and Precautions (5.2).]
- Fenoglide is contraindicated in nursing mothers [see Use in Specific Populations (8.3).]
- Fenoglide is contraindicated in patients who have a known hypersensitivity to fenofibrate, such as severe skin rashes, including Stevens-Johnson syndrome and toxic epidermal necrolysis. [see Warnings and Precautions (5.9).]

5 WARNINGS AND PRECAUTIONS

5.1 Liver Tests

Fenofibrate at doses equivalent to 87 mg to 130 mg fenofibrate per day [at the highest dose, comparable to Fenoglide, 120 mg] can increase serum transaminases [AST (SGOT) or ALT (SGPT)].

In a pooled analysis of 10 placebo-controlled trials, increases to >3 times the upper limit of normal occurred in 5.3% of patients taking fenofibrate versus 1.1% of patients treated with placebo.

When transaminase determinations were followed either after discontinuation of treatment or during continued treatment, a return to normal limits was usually observed. The incidence of increases in transaminases related to fenofibrate therapy appear to be dose related. In an 8-week dose-ranging study, the incidence of ALT or AST elevations to at least three times the upper limit of normal was 13% in patients receiving dosages equivalent to 87 mg to 130 mg fenofibrate per day and was 0% in those receiving dosages equivalent to 43 mg or less fenofibrate per day, or placebo. Hepatocellular, chronic active and cholestatic hepatitis have been reported after exposures of weeks to several years. In extremely rare cases, cirrhosis has been reported in association with chronic active hepatitis.

Regular periodic monitoring of liver tests, including serum ALT (SGPT) should be performed for the duration of therapy with Fenoglide, and therapy discontinued if enzyme levels persist above three times the normal limit.

5.2 Cholelithiasis

Fenofibrate increases cholesterol excretion into the bile, leading to risk of cholelithiasis. If cholelithiasis is suspected, gallbladder studies are indicated. Fenoglide therapy should be discontinued if gallstones are found.

5.3 Concomitant Coumarin Anticoagulants

Caution should be exercised when anticoagulants are given in conjunction with Fenoglide because of the potentiation of coumarin-type anti-coagulants in prolonging the prothrombin time/INR. The dosage of the anticoagulant should be reduced to maintain the prothrombin time/INR at the desired level to prevent bleeding complications. Frequent prothrombin time/INR determinations are advisable until it has been definitely determined that the prothrombin time/INR has stabilized. [See Drug Interactions (7.1).]

5.4 Skeletal Muscle

Treatment with fenofibrate increases risk of myopathy. Treatment with fenofibrate increases risk of rhabdomyolysis, usually in patients with impaired renal function. Myopathy should be considered in any patient with diffuse myalgias, muscle tenderness or weakness, and/or marked elevations of creatine phosphokinase (CPK) levels.

Patients should be advised to report promptly unexplained muscle pain, tenderness or weakness, particularly if accompanied by malaise or fever. CPK levels should be assessed in patients reporting these symptoms, and fenofibrate therapy should be discontinued if markedly elevated CPK levels occur or myopathy is diagnosed.

5.5 Serum Creatinine

Elevations in serum creatinine have been reported in patients on fenofibrate. These elevations tend to return to baseline following discontinuation of fenofibrate. The clinical significance of these observations is unknown.

5.6 Mortality and Coronary Heart Disease Morbidity

The Fenofibrate Intervention and Event Lowering in Diabetes (FIELD) study was a 5-year randomized, placebo-controlled study of 9,795 patients with type 2 diabetes mellitus treated with fenofibrate. Fenofibrate demonstrated a non-significant 11% relative reduction in the primary outcome of coronary heart disease events (hazard ratio [HR] 0.89, 95% CI 0.75-1.05, p=0.16) and a significant 11% reduction in the secondary outcome of total cardiovascular disease events (HR 0.89 [0.80-0.99], p=0.04). There was a non-significant 11% (HR 1.11 [0.95, 1.29], p=0.18) and 19% (HR 1.19 [0.90, 1.57], p=0.22) increase in total and coronary heart disease mortality, respectively, with fenofibrate as compared to placebo.

In the Coronary Drug Project, a large study of post myocardial infarction of patients treated for 5 years with clofibrate, there was no difference in mortality seen between the clofibrate group and the placebo group.

In a study conducted by the World Health Organization (WHO), 5000 subjects without known coronary artery disease were treated with placebo or clofibrate for 5 years and followed for an additional one year. There was a statistically significant, higher age-adjusted all-cause mortality in the clofibrate group compared with the placebo group (5.70% vs. 3.96%, p=<0.01). Excess mortality was due to a 33% increase in non-cardiovascular causes, including malignancy, post-cholecystectomy complications, and pancreatitis. This appeared to confirm the higher risk of gallbladder disease seen in clofibrate-treated patients studied in the Coronary Drug Project.

The Helsinki Heart Study was a large (n=4,081) study of middle-aged men without a history of coronary artery disease. Subjects received either placebo or gemfibrozil for 5 years, with a 3.5 year open extension afterward. Total mortality was numerically higher in the gemfibrozil randomization group but did not achieve statistical significance (p=0.19, 95% confidence interval for relative risk G:P=0.91-1.64). Although cancer deaths trended higher in the gemfibrozil group (p=0.11), cancers (excluding basal cell carcinoma) were diagnosed with equal frequency in both study groups. Due to the limited size of the study, the relative risk of death from any cause was not shown to be different than that seen in the 9 year follow-up data from the WHO study (RR=1.29).

A secondary prevention component of the Helsinki Heart Study enrolled middle-aged men excluded from the primary prevention study because of known or suspected coronary heart disease. Subjects received gemfibrozil or placebo for 5 years. Although cardiac deaths trended higher in the gemfibrozil group, this was not statistically significant (hazard ratio 2.2, 95% confidence interval: 0.94-5.05).

5.7 Pancreatitis

Pancreatitis has been reported in patients taking fenofibrate. This occurrence may represent a failure of efficacy in patients with severe hypertriglyceridemia, a direct drug effect, or a secondary phenomenon mediated through biliary tract stone or sludge formation with obstruction of the common bile duct.

5.8 Venothromboembolic Disease

In the FIELD trial, pulmonary embolus (PE) and deep vein thrombosis (DVT) were observed at higher rates in the fenofibrate- than the placebo-treated group. Of 9,795 patients enrolled in FIELD, there were 4,900 in the placebo group and 4,895 in the fenofibrate group. For DVT, there were 48 events (1%) in the placebo group and 67 (1%) in the fenofibrate group (p = 0.074); and for PE, there were 32 (0.7%) events in the placebo group and 53 (1%) in the fenofibrate group (p = 0.022).

In the Coronary Drug Project, a higher proportion of the clofibrate group experienced definite or suspected fatal or nonfatal pulmonary embolism or thrombophlebitis than the placebo group (5.2% vs. 3.3% at five years; p < 0.01).

5.9 Hypersensitivity Reactions

Acute hypersensitivity reactions including severe skin rashes requiring patient hospitalization and treatment with steroids have occurred rarely during treatment with fenofibrate, including rare spontaneous reports of Stevens-Johnson syndrome, and toxic epidermal necrolysis.

5.10 Hematologic Changes

Mild to moderate hemoglobin, hematocrit, and white blood cell decreases have been observed in patients following initiation of fenofibrate therapy.

5.11 Concomitant HMG-CoA Reductase Inhibitors

The combined use of fenofibric acid derivatives, particularly gemfibrozil, and HMG-CoA reductase inhibitors results in an increased risk of rhabdomyolysis and myoglobinuria leading in a high proportion of cases to acute renal failure.

The combined use of Fenoglide and HMG-CoA reductase inhibitors should be avoided unless the benefit of further alterations in lipid levels is likely to outweigh the increased risk of this drug combination. [see Drug Interactions (7.3).]

6 ADVERSE REACTIONS

6.1 Clinical Studies Experience

Because clinical studies are conducted under widely varying conditions, adverse reaction rates observed in the clinical studies of a drug cannot be directly compared to rates in the clinical studies of another drug and may not reflect rates observed in clinical practice.

Adverse reactions reported by 2% or more of patients treated with fenofibrate and greater than placebo during double-blind, placebo-controlled trials are listed in Table 1. Adverse reactions led to discontinuation of treatment in 5.0% of patients treated with fenofibrate and in 3.0% treated with placebo. Increases in liver tests were the most frequent events, causing discontinuation of fenofibrate treatment in 1.6% of patients in double-blind trials.

Table 1. Adverse Reactions Reported by 2% or More of Patients Treated with Fenofibrate and Greater than Placebo During the Double-Blind, Placebo-Controlled Trials
BODY SYSTEM Adverse Reaction | Fenofibrate [Dosage equivalent to 130 mg fenofibrate] (N=439) | Placebo (N=365)
BODY AS A WHOLE
Abdominal Pain | 4.6% | 4.4%
Back Pain | 3.4% | 2.5%
Headache | 3.2% | 2.7%
DIGESTIVE
Nausea | 2.3% | 1.9%
Constipation | 2.1% | 1.4%
INVESTIGATIONS
Abnormal Liver Tests | 7.5% | 1.4%
Increased AST | 3.4% | 0.5%
Increased ALT | 3.0% | 1.6%
Increased Creatine Phosphokinase | 3.0% | 1.4%
RESPIRATORY
Respiratory Disorder | 6.2% | 5.5%
Rhinitis | 2.3% | 1.1%

6.2 Postmarketing Experience

The following adverse reactions have been identified during postapproval use of fenofibrate: myalgia, rhabdomyolysis, increased creatinine phosphokinase, pancreatitis, increased alanine aminotransaminase, increased aspartate aminotransaminase, renal failure, muscle spasms, acute renal failure, hepatitis, cirrhosis, nausea, abdominal pain, anemia, headache, arthralgia, and asthenia. Because these reactions are reported voluntarily from a population of uncertain size, it is not always possible to reliably estimate their frequency or establish a casual relationship to drug exposure.

7 DRUG INTERACTIONS

7.1 Coumarin Anticoagulants

Caution should be exercised when coumarin anticoagulants are given in conjunction with Fenoglide. The dosage of the anticoagulants should be reduced to maintain the prothrombin time/INR at the desired level to prevent bleeding complications. Frequent prothrombin time/INR determinations are advisable until it has been definitely determined that the prothrombin time/INR has stabilized. [see Concomitant Coumarin Anticoagulants (5.3).]

7.2 Cyclosporine

Because cyclosporine can produce nephrotoxicity with decreases in creatinine clearance and rises in serum creatinine, and because renal excretion is the primary elimination route of fibrate drugs including Fenoglide, there is a risk that an interaction will lead to deterioration of renal function. The benefits and risks of using Fenoglide with immunosuppressants and other potentially nephrotoxic agents should be carefully considered, and the lowest effective dose employed.

7.3 HMG-CoA Reductase Inhibitors

The combined use of fenofibric acid derivatives, particularly gemfibrozil, and HMG-CoA reductase inhibitors results in an increased risk of rhabdomyolysis and myoglobinuria leading in a high proportion of cases to acute renal failure. [See Concomitant HMG-CoA Reductase Inhibitors (5.11).]

The combined use of Fenoglide and HMG-CoA reductase inhibitors should be avoided unless the benefit of further alterations in lipid levels is likely to outweigh the increased risk of this drug combination.

In a single-dose drug interaction study in 23 healthy adults the concomitant administration of fenofibrate and pravastatin resulted in no clinically important difference in the pharmacokinetics of fenofibric acid, pravastatin, or its active metabolite 3α-hydroxy iso-pravastatin when compared to either drug given alone.

7.4 Bile-Acid Resins

Since bile acid sequestrants may bind other drugs given concurrently, patients should take Fenoglide at least 1 hour before or 4-6 hours after a bile acid binding resin to avoid impeding its absorption.

8 USE IN SPECIFIC POPULATIONS

8.1 Pregnancy

Fenofibrate is classified as pregnancy category C. Fenofibrate has been shown to be embryocidal and teratogenic in rats when given in doses 7 to 10 times the maximum recommended human dose and embryocidal in rabbits when given at 9 times the maximum recommended human dose (on the basis of mg/meter^2 surface area). There are no adequate and well-controlled studies in pregnant women. Fenofibrate should be used during pregnancy only if the potential benefit justifies the potential risk to the fetus. [see Nonclinical Toxicology (13).]

8.3 Nursing Mothers

Fenofibrate should not be used in nursing mothers. Because of the potential for tumorigenicity seen in animal studies, a decision should be made whether to discontinue nursing or to discontinue the drug.

8.4 Pediatric Use

Safety and efficacy in pediatric patients have not been established.

8.5 Geriatric Use

Fenofibric acid exposure is not influenced by age. However, elderly patients have a higher incidence of renal impairment. Dose selection for the elderly should be made on the basis of renal function.

8.6 Renal Impairment

Fenofibric acid is known to be substantially excreted by the kidney, and the risk of adverse reactions to this drug may be greater in patients with impaired renal function. Fenofibrate should be avoided in patients with severe renal impairment and dose reduction is required in patients with mild to moderate renal impairment.

10 OVERDOSAGE

There is no specific treatment for overdose with Fenoglide. General supportive care of the patient is indicated, including monitoring of vital signs and observation of clinical status, should an overdose occur. If indicated, elimination of unabsorbed drug should be achieved by emesis or gastric lavage; usual precautions should be observed to maintain the airway. Because fenofibrate is highly bound to plasma proteins, hemodialysis should not be considered.

11 DESCRIPTION

Fenoglide (fenofibrate) Tablets, is a lipid regulating agent available as tablets for oral administration. Each tablet contains 40 mg or 120 mg fenofibrate. The chemical name for fenofibrate is 2-[4-(4-chlorobenzoyl) phenoxy]-2-methyl-propanoic acid, 1-methylethyl ester with the following structural formula:

The empirical formula is C20H21O4Cl and the molecular weight is 360.83; fenofibrate is insoluble in water. The melting point is 79° to 82°C. Fenofibrate is a white solid which is stable under ordinary conditions.

Inactive Ingredients: Each tablet contains lactose monohydrate, NF; Polyethylene Glycol 6000, NF; Poloxamer 188, NF; and magnesium stearate, NF.

12 CLINICAL PHARMACOLOGY

12.1 Mechanism of Action

The effects of fenofibric acid seen in clinical practice have been explained in vivo in transgenic mice and in vitro in human hepatocyte cultures by the activation of peroxisome proliferator activated receptor α (PPARα).

Through this mechanism, fenofibrate increases lipolysis and elimination of triglyceride-rich particles from plasma by activating lipoprotein lipase and reducing production of apoprotein C-III (an inhibitor of lipoprotein lipase activity). The resulting fall in triglycerides produces an alteration in the size and composition of LDL from small, dense particles (which are thought to be atherogenic due to their susceptibility to oxidation), to large buoyant particles. These larger particles have a greater affinity for cholesterol receptors and are catabolized rapidly. Activation of PPARα also induces an increase in the synthesis of apoproteins A-I, A-II and HDL-cholesterol.

Fenofibrate also reduces serum uric acid levels in hyperuricemic and normal individuals by increasing the urinary excretion of uric acid.

12.2 Pharmacodynamics

A variety of clinical studies have demonstrated that elevated levels of total cholesterol (total-C), low density lipoprotein cholesterol (LDL-C), and apolipoprotein B (apo B), an LDL membrane complex, are risk factors for human atherosclerosis. Similarly, decreased levels of high density lipoprotein cholesterol (HDL-C) and its transport complex, apolipoprotein A (apo AI and apo AII) are risk factors for the development of atherosclerosis. Epidemiologic investigations have established that cardiovascular morbidity and mortality vary directly with the level of total-C, LDL-C, and triglycerides, and inversely with the level of HDL-C. The independent effect of raising HDL-C or lowering triglycerides (TG) on the risk of cardiovascular morbidity and mortality has not been determined.

Fenofibric acid, the active metabolite of fenofibrate, produces reductions in total cholesterol, LDL cholesterol, apolipoprotein B, total triglycerides, and triglyceride-rich lipoprotein (VLDL) in treated patients. In addition, treatment with fenofibrate results in increases in high density lipoprotein (HDL) and apoproteins apo AI and apo AII.

12.3 Pharmacokinetics

Plasma concentrations of fenofibric acid after single-dose administration of Fenoglide (fenofibrate) Tablets, 120 mg are equivalent to those of Fenofibrate 130 mg capsules under high-fat conditions.

A high-fat meal did not affect the fenofibric acid AUC after Fenoglide administration but did increase the mean Cmax by 44% compared to fasting conditions.

- Absorption: The absolute bioavailability of fenofibrate cannot be determined as the compound is virtually insoluble in aqueous media suitable for injection. However, Fenoglide is well absorbed from the gastrointestinal tract. Following oral administration in healthy volunteers, approximately 60% of a single dose of radiolabelled fenofibrate appeared in urine, primarily as fenofibric acid and its glucuronate conjugate, and 25% was excreted in the feces. Peak plasma levels of fenofibric acid from Fenoglide occur, on average, within 2 to 3 hours after administration.
  Doses of three Fenoglide (fenofibrate) Tablets, 40 mg are considered to be equivalent to single doses of Fenoglide (fenofibrate) Tablets, 120 mg.
- Distribution: In healthy volunteers, steady-state plasma levels of fenofibric acid were shown to be achieved within a week of dosing and did not demonstrate accumulation across time following multiple dose administration. Serum protein binding was approximately 99% in normal and hyperlipidemic subjects.
- Metabolism: Following oral administration, fenofibrate is rapidly hydrolyzed by esterases to the active metabolite, fenofibric acid; no unchanged fenofibrate is detected in plasma.
  Fenofibric acid is primarily conjugated with glucuronic acid and then excreted in urine. A small amount of fenofibric acid is reduced at the carbonyl moiety to a benzhydrol metabolite which is, in turn, conjugated with glucuronic acid and excreted in urine.
  In vivo metabolism data indicate that neither fenofibrate nor fenofibric acid undergo oxidative metabolism (e.g., cytochrome P450) to a significant extent.
- Excretion: After absorption, fenofibrate is mainly excreted in the urine in the form of metabolites, primarily fenofibric acid and fenofibric acid glucuronide. After administration of radiolabelled fenofibrate, approximately 60% of the dose appeared in the urine and 25% was excreted in the feces.
  Fenofibric acid from Fenoglide is eliminated with a half-life of 23 hours, allowing once daily administration in a clinical setting.
- Geriatrics: In elderly volunteers 77 to 87 years of age, the oral clearance of fenofibric acid following a single oral dose of fenofibrate was 1.2 L/h, which compares to 1.1 L/h in young adults. This indicates that a similar dosage regimen can be used in the elderly, without increasing accumulation of the drug or metabolites. [See Dosage and Administration (2.4) and Use in Specific Populations (8.5).]
- Pediatrics: Fenoglide has not been investigated in adequate and well-controlled trials in pediatric patients.
- Gender: No pharmacokinetic difference between males and females has been observed for fenofibrate.
- Race: The influence of race on the pharmacokinetics of fenofibrate has not been studied; however, fenofibrate is not metabolized by enzymes known for exhibiting inter-ethnic variability. Therefore, inter-ethnic pharmacokinetic differences are very unlikely.
- Renal Insufficiency: The pharmacokinetics of fenofibric acid was examined in patients with mild, moderate, and severe renal impairment. Patients with severe renal impairment (creatinine clearance [CrCl] ≤ 30 mL/min or estimated glomerular filtration rate [eGFR] < 30 mL/min/1.73m^2) showed 2.7-fold increase in exposure for fenofibric acid and increased accumulation of fenofibric acid during chronic dosing compared to that of healthy subjects. Patients with mild to moderate renal impairment (CrCl 30-80 mL/min or eGFR 30-59 mL/min/1.73m^2) had similar exposure but an increase in the half-life for fenofibric acid compared to that of healthy subjects. Based on these findings, the use of Fenoglide should be avoided in patients who have severe renal impairment and dose reduction is required in patients having mild to moderate renal impairment. [See Dosage and Administration (2.3).]
- Hepatic Insufficiency: No pharmacokinetic studies have been conducted in patients having hepatic insufficiency.
- Drug-Drug Interactions: In vitro studies using human liver microsomes indicate that fenofibrate and fenofibric acid are not inhibitors of cytochrome (CYP) P450 isoforms CYP3A4, CYP2D6, CYP2E1, or CYP1A2. They are weak inhibitors of CYP2C19 and CYP2A6, and mild-to-moderate inhibitors of CYP2C9 at therapeutic concentrations.
  Potentiation of coumarin-type anticoagulants has been observed with prolongation of the prothrombin time/INR. [See Concomitant Coumarin Anticoagulants (5.3).]
  Bile-acid resins have been shown to bind other drugs given concurrently. Therefore, fenofibrate should be taken at least 1 hour before or 4 to 6 hours after a bile acid binding resin to avoid impeding its absorption. [See Drug Interactions (7.4).]

13 NONCLINICAL TOXICOLOGY

13.1 Carcinogenesis, Mutagenesis, Impairment of Fertility

In a 24-month study in rats (10, 45, and 200 mg/kg; 0.3, 1, and 6 times the maximum recommended human dose on the basis of mg/meter^2 of surface area), the incidence of liver carcinoma was significantly increased at 6 times the maximum recommended human dose in males and females. A statistically significant increase in pancreatic carcinomas occurred in males at 1 and 6 times the maximum recommended human dose; there were also increases in pancreatic adenomas and benign testicular interstitial cell tumors at 6 times the maximum recommended human dose in males. In a second 24-month study in a different strain of rats (doses of 10 and 60 mg/kg; 0.3 and 2 times the maximum recommended human dose based on mg/meter^2 surface area), there were significant increases in the incidence of pancreatic acinar adenomas in both sexes and increases in interstitial cell tumors of the testes at 2 times the maximum recommended human dose.

A comparative carcinogenicity study was done in rats comparing three drugs: fenofibrate (10 and 70 mg/kg; 0.3 and 1.6 times the maximum recommended human dose), clofibrate (400 mg/kg; 1.6 times the human dose), and gemfibrozil (250 mg/kg; 1.7 times the human dose) (multiples based on mg/meter^2 surface area). Pancreatic acinar adenomas were increased in males and females on fenofibrate; hepatocellular carcinoma and pancreatic acinar adenomas were increased in males and hepatic neoplastic nodules in females treated with clofibrate; hepatic neoplastic nodules were increased in males and females treated with gemfibrozil while testicular interstitial cell tumors were increased in males on all three drugs.

In a 21-month study in mice at doses of 10, 45, and 200 mg/kg (approximately 0.2, 0.7 and 3 times the maximum recommended human dose on the basis of mg/meter^2 surface area), there were statistically significant increases in liver carcinoma at 3 times the maximum recommended human dose in both males and females. In a second 18-month study at the same doses, there was a significant increase in liver carcinoma in male mice and liver adenoma in female mice at 3 times the maximum recommended human dose.

Electron microscopy studies have demonstrated peroxisomal proliferation following fenofibrate administration to the rat. An adequate study to test for peroxisome proliferation in humans has not been done, but changes in peroxisome morphology and numbers have been observed in humans after treatment with other members of the fibrate class when liver biopsies were compared before and after treatment in the same individual.

Fenofibrate has been demonstrated to be devoid of mutagenic potential in the following tests: Ames, mouse lymphoma, chromosomal aberration, and unscheduled DNA synthesis.

Administration of 9 times the maximum recommended human dose of fenofibrate to female rats before and throughout gestation caused 100% of dams to delay delivery and resulted in a 60% increase in post-implantation loss, a decrease in litter size, a decrease in birth weight, a 40% survival of pups at birth, a 4% survival of pups as neonates, and a 0% survival of pups to weaning, and an increase in spina bifida.

Administration of 10 times the maximum recommended human dose to female rats on days 6-15 of gestation caused an increase in gross, visceral and skeletal findings in fetuses (domed head/hunched shoulders/rounded body/abnormal chest, kyphosis, stunted fetuses, elongated sternal ribs, malformed sternebrae, extra foramen in palatine, misshapen vertebrae, supernumerary ribs).

Administration of 7 times the maximum recommended human dose to female rats from day 15 of gestation through weaning caused a delay in delivery, a 40% decrease in live births, a 75% decrease in neonatal survival, and decreases in pup weight, at birth as well as on days 4 and 21 post-partum.

Administration of 9 and 18 times the maximum recommended human dose to female rabbits caused abortions in 10% of dams at 9 times and 25% of dams at 18 times the maximum recommended human dose and death of 7% of fetuses at 18 times the maximum recommended human dose.

14 CLINICAL STUDIES

14.1 Hyperlipidemia (Heterozygous Familial and Nonfamilial) and Mixed Dyslipidemia

The effects of fenofibrate at a dose equivalent to 120 mg Fenoglide per day were assessed from four randomized, placebo-controlled, double-blind, parallel-group studies including patients with the following mean baseline lipid values: total-C 306.9 mg/dL; LDL-C 213.8 mg/dL; HDL-C 52.3 mg/dL; and triglycerides 191.0 mg/dL. Fenofibrate therapy lowered LDL-C, Total-C, and the LDL-C/HDL-C ratio. Fenofibrate therapy also lowered triglycerides and raised HDL-C (see Table 2).

Table 2. Mean Percent Change in Lipid Parameters at End of Treatment [Duration of study treatment was 3 to 6 months.]
Treatment Group | Total-C | LDL-C | HDL-C | TG
Pooled Cohort
Mean baseline lipid values (n=646) | 306.9 mg/dL | 213.8 mg/dL | 52.3 mg/dL | 191.0 mg/dL
All FEN (n=361) | -18.7% [p=<0.05 vs. placebo] | -20.6% | +11.0% | -28.9%
Placebo (n=285) | -0.4% | -2.2% | +0.7% | +7.7%
Baseline LDL-C >160 mg/dL and TG <150 mg/dL (Type IIa)
Mean baseline lipid values (n=334) | 307.7 mg/dL | 227.7 mg/dL | 58.1 mg/dL | 101.7 mg/dL
All FEN (n=193) | -22.4% | -31.4% | +9.8% | -23.5%
Placebo (n=141) | +0.2% | -2.2% | +2.6% | +11.7%
Baseline LDL-C >160 mg/dL and TG ≥150 mg/dL (Type IIb)
Mean baseline lipid values (n=242) | 312.8 mg/dL | 219.8 mg/dL | 46.7 mg/dL | 231.9 mg/dL
All FEN (n=126) | -16.8% | -20.1% | +14.6% | -35.9%
Placebo (n=116) | -3.0% | -6.6% | +2.3% | +0.9%

In a subset of the subjects, measurements of apo B were conducted. Fenofibrate treatment significantly reduced apo B from baseline to endpoint as compared with placebo (-25.1% vs. 2.4%, p<0.0001, n=213 and 143 respectively).

14.2 Hypertriglyceridemia

The effects of fenofibrate on serum triglycerides were studied in two randomized, double-blind, placebo-controlled clinical trials of 147 hypertriglyceridemic patients. Patients were treated for eight weeks under protocols that differed only in that one entered patients with baseline triglyceride (TG) levels of 500 to 1500 mg/dL, and the other TG levels of 350 to 500 mg/dL. In patients with hypertriglyceridemia and normal cholesterolemia with or without hyperchylomicronemia, treatment with fenofibrate at dosages equivalent to 120 mg Fenoglide (fenofibrate) Tablets per day decreased primarily very low density lipoprotein (VLDL) triglycerides and VLDL cholesterol. Treatment of patients with elevated triglycerides often results in an increase of low density lipoprotein (LDL) cholesterol (see Table 3).

Table 3. Effects of Fenofibrate in Patients With Hypertriglyceridemia
Study 1 | Placebo |  |  |  | Fenofibrate
Baseline TG levels 350 to 499 mg/dL | N | Baseline (Mean) | Endpoint (Mean) | % Change (Mean) | N | Baseline (Mean) | Endpoint (Mean) | % Change (Mean)
Triglycerides | 28 | 449 | 450 | -0.5 | 27 | 432 | 223 | -46.2 [=p<0.05 vs. placebo]
VLDL Triglycerides | 19 | 367 | 350 | 2.7 | 19 | 350 | 178 | -44.1
Total Cholesterol | 28 | 255 | 261 | 2.8 | 27 | 252 | 227 | -9.1
HDL Cholesterol | 28 | 35 | 36 | 4 | 27 | 34 | 40 | 19.6
LDL Cholesterol | 28 | 120 | 129 | 12 | 27 | 128 | 137 | 14.5
VLDL Cholesterol | 27 | 99 | 99 | 5.8 | 27 | 92 | 46 | -44.7
Study 2 | Placebo |  |  |  | Fenofibrate
Baseline TG levels 500 to 1500 mg/dL | N | Baseline (Mean) | Endpoint (Mean) | % Change (Mean) | N | Baseline (Mean) | Endpoint (Mean) | % Change (Mean)
Triglycerides | 44 | 710 | 750 | 7.2 | 48 | 726 | 308 | -54.5
VLDL Triglycerides | 29 | 537 | 571 | 18.7 | 33 | 543 | 205 | -50.6
Total Cholesterol | 44 | 272 | 271 | 0.4 | 48 | 261 | 223 | -13.8
HDL Cholesterol | 44 | 27 | 28 | 5.0 | 48 | 30 | 36 | 22.9
LDL Cholesterol | 42 | 100 | 90 | -4.2 | 45 | 103 | 131 | 45.0
VLDL Cholesterol | 42 | 137 | 142 | 11.0 | 45 | 126 | 54 | -49.4

16 HOW SUPPLIED/STORAGE AND HANDLING

- NDC 52725-490-90: 40 mg White to off-white oval tablets. Debossed "FLO"; bottle of 90 tablets
- NDC 52725-495-90: 120 mg White to off-white oval tablets. Debossed "FHI"; bottle of 90 tablets

STORAGE AND HANDLING

Store at 25°C (77°F); excursions permitted to 15°-30°C (59°-86°F) [See USP Controlled Room Temperature].

Distributed by:
Shore Therapeutics, Inc.
Stamford, CT 06901

FEN-TPI-07 Rev. 10/2010

PRINCIPAL DISPLAY PANEL - 90 Tablet Bottle Label

NDC 52725-490-90
90 Tablets

Rx only

Fenoglide®
(fenofibrate)
tablets

40 mg

Distributed by: Shore Therapeutics, Inc.
Stamford, CT 06901

PRINCIPAL DISPLAY PANEL - 90 Tablet Bottle Label

NDC 52725-495-90
90 Tablets

Rx only

Fenoglide®
(fenofibrate)
tablets

120 mg

Distributed by:
Shore Therapeutics, Inc.
Stamford, CT 06901